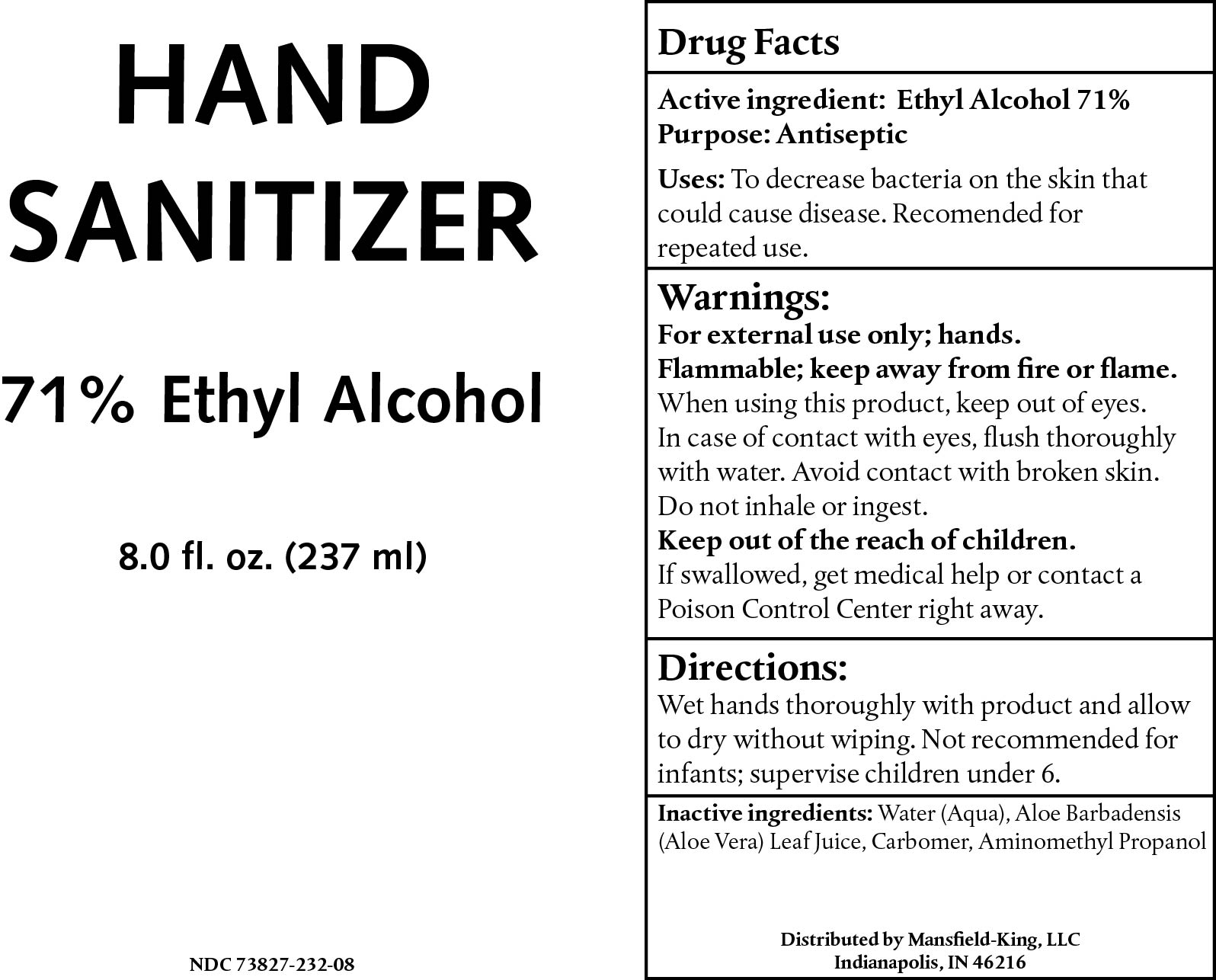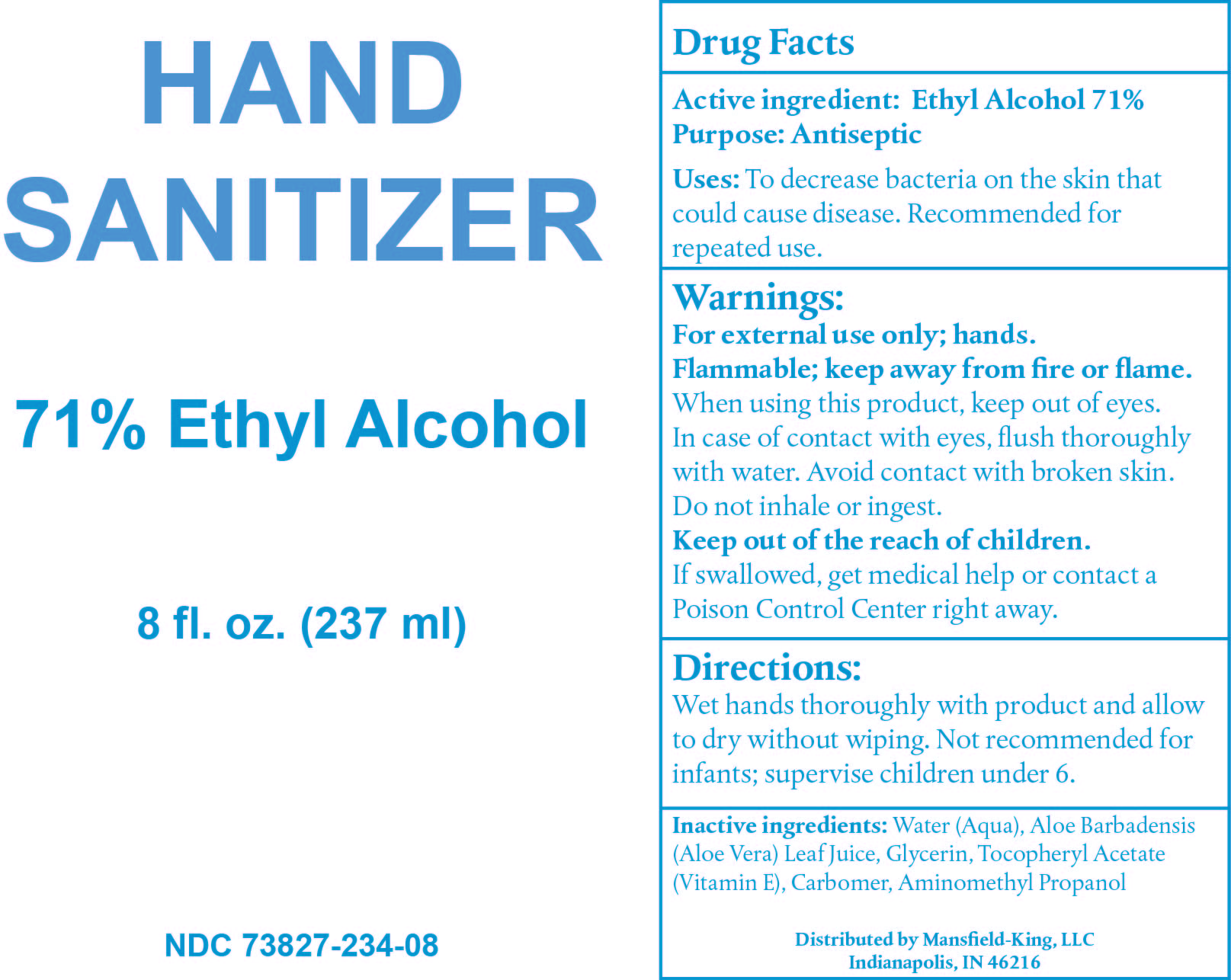 DRUG LABEL: Hand Sanitizer
NDC: 73827-234 | Form: GEL
Manufacturer: Mansfield-King, LLC
Category: otc | Type: HUMAN OTC DRUG LABEL
Date: 20200505

ACTIVE INGREDIENTS: ALCOHOL 75.768575 mL/100 mL
INACTIVE INGREDIENTS: WATER 21.59706003 mL/100 mL; AMINOMETHYLPROPANOL 0.315521488 mL/100 mL; GLYCERIN 0.334123662 mL/100 mL; CARBOMER INTERPOLYMER TYPE A (55000 CPS) 0.300711296 mL/100 mL; ALOE VERA LEAF 1.683983259 mL/100 mL; .ALPHA.-TOCOPHEROL ACETATE 0.0000252597 mL/100 mL

Hand sanitizer

Active Ingredient(s)

alcohol; 72% w/w

Purpose

Antiseptic; Hand Sanitizer

Use

To decrease bacteria on the skin that could cause disease. Recomended for repeated use.

Warnings

For external use only; hands. Flammable; keep away from fire or flame. When using this product, keep out of eyes. In case of contact with eyes, flush thoroughly with water. Avoid contact with broken skin. Do not inhale or ingest.

Do not use

Not recommended for infants; supervise children under 6.

When using this product, keep out of eyes. In case of contact with eyes, flush thoroughly with water. Avoid contact with broken skin. Do not inhale or ingest. Keep out of the reach of children. If swallowed, get medical help or contact a Poison Control Center right away.

KEEP OUT OF REACH OF CHILDREN

Keep out of the reach of children. If swallowed, get medical help or contact a Poison Control Center right away.

Directions

Wet hands thoroughly with product and allow to dry without wiping. Not recommended for infants; supervise children under 6.

STORAGE AND HANDLING

Flammable; keep away from fire or flame.

Inactive ingredients

Water (Aqua), Aloe Barbadensis (Aloe Vera) Leaf Juice, Glycerin, Fragrance, Carbomer, Aminomethyl Propanol

Package Label - Principal Display Panel

237 mL. NDC 73827-225-08